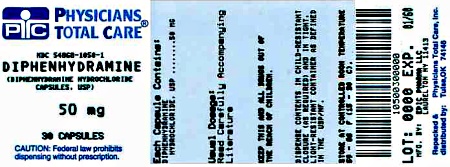 DRUG LABEL: diphenhydramine hydrochloride
NDC: 54868-1050 | Form: CAPSULE
Manufacturer: Physicians Total Care, Inc.
Category: otc | Type: HUMAN OTC DRUG LABEL
Date: 20120605

ACTIVE INGREDIENTS: DIPHENHYDRAMINE HYDROCHLORIDE 50 mg/1 1
INACTIVE INGREDIENTS: SILICON DIOXIDE; STARCH, CORN; D&C RED NO. 28; FD&C BLUE NO. 1; FD&C RED NO. 40; GELATIN; ANHYDROUS LACTOSE; MAGNESIUM STEARATE; SILICON DIOXIDE; SODIUM LAURYL SULFATE

Drug Facts

Active ingredient (in each capsule)

Diphenhydramine Hydrochloride 25 mg

Diphenhydramine Hydrochloride 50 mg

Purpose

Antihistamine

Uses

Temporarily relieves these symptoms due to hay fever or other upper respiratory allergies

- runny nose and sneezing
- itching of the nose or throat
- itchy, watery eyes.

Warnings

Ask a doctor before use if you have

- a breathing problem such as emphysema or chronic bronchitis
- glaucoma
- difficulty in urination due to enlargement of the prostate gland

Do not use with ny other product containing diphenhydramine, including products used topically.

Ask a doctor or pharmacist before use if you are

- taking tranquilizers or sedatives
- taking other products containing diphenhydramine

When using this product

- Do not exceed recommended dosage
- excitability may occur, especially in children
- marked drowsiness may occur
- alcohol, sedatives, and tranquilizers may increase drowsiness
- avoid alcoholic drinks
- use caution when driving a motor vehicle or operating machinery

If pregnant or breastfeeding ask a health professional before use.

Keep out of the reach of children.

In case of overdose, get medical help or contact a Poison Control Center right away.

Directions

- Adults and Children 12 years and over: 25 to 50 mg (1 to 2 capsules) every 4 to 6 hours, not to exceed 12 capsules in 24 hours.
- Children 12 years and under: Consult a Doctor

Inactive ingredients

Colloidal Silicon Dioxide, Corn Starch, D&C Red #28, FD&C Blue #1, FD&C Red #40, Gelatin, Anhydrous Lactose, Magnesium Stearate, Silicon Dioxide and Sodium Lauryl Sulfate.

Storage and Handling

Keep tightly closed. Store at 20º to 25ºC (68º to 77ºF) [See USP Controlled Room Temperature].

Manufactured for Sandoz Inc.

Princeton, NJ 08540

Manufactured by Epic Pharma, LLC

Laurelton, NY 11413

L1812

Rev. 11/08

Relabeling and Repackaging by:
Physicians Total Care, Inc.
Tulsa, Oklahoma 74146

HOW SUPPLIED

DiphenhydrAMINE Hydrochloride Capsules USP
50 mg

Bottles of 30 | NDC 54868-1050-1
Bottles of 100 | NDC 54868-1050-5

Package Label - Principal Display Panel

NDC 54868-1050-1

DiphenhydrAMINE

Hydrochloride

Capsules USP

50 mg

30 Capsules